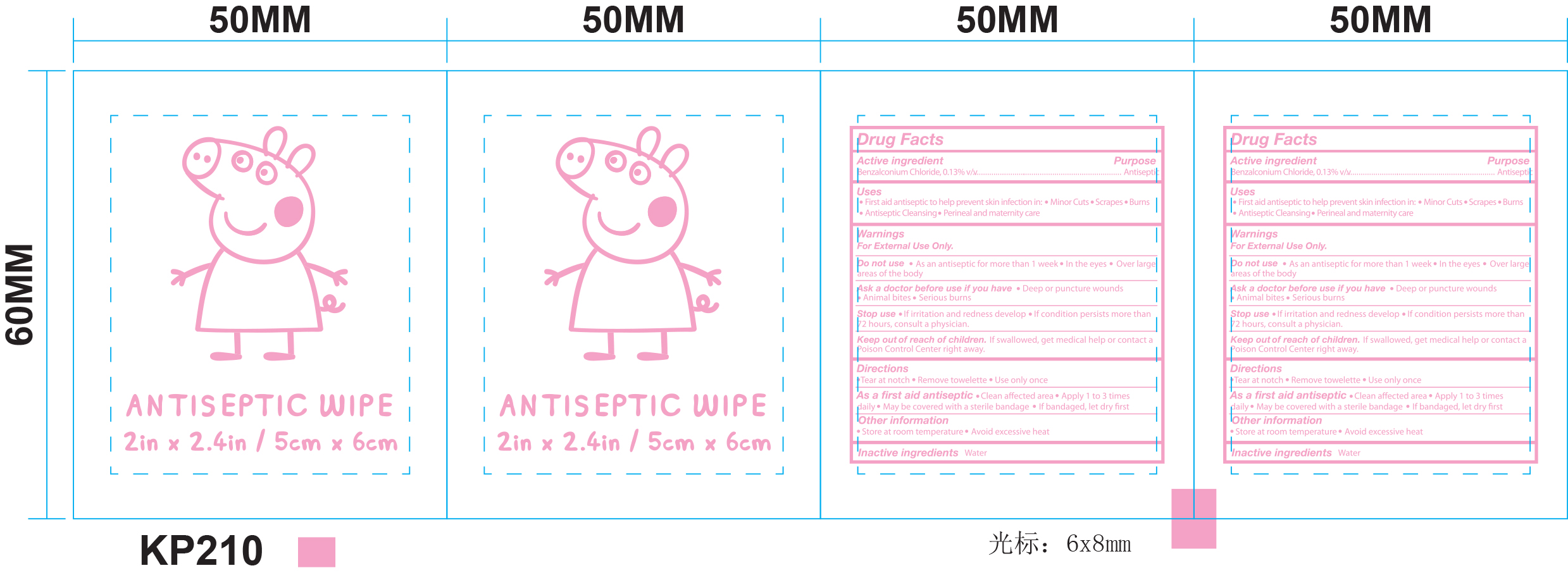 DRUG LABEL: ANTISEPTIC WIPE
NDC: 70108-100 | Form: CLOTH
Manufacturer: Ashtel Studios Inc.
Category: otc | Type: HUMAN OTC DRUG LABEL
Date: 20201203

ACTIVE INGREDIENTS: BENZALKONIUM CHLORIDE 0.133 g/100 g
INACTIVE INGREDIENTS: WATER

ACTIVE INGREDIENT

Benzalkonium Chloride 0.13% v/v

Purpose

Antiseptic

PURPOSE

First aid antiseptic to help prevent skin infection in:

- Minor Cuts
- Scrapes
- Burns
- Antiseptic Cleasing
- Perineal and maternity care

WARNINGS

For External Use Only.

Do not use

- As an antiseptic for more than 1 week
- In the eyes
- Over large areas of the body

Ask a doctor before use if you have

- Deep or pucture wounds
- Animal bites
- Serious burns

Stop use

- If irritation and redness develop
- If condition persists more than 72 hours, consult a physician.

Keep out of reach of children.

If swallowed, get medical help or contact a Poison Control Center right away.

Directions

- Tear at notch
- Remove towelette
- Use only once

As a first aid antiseptic

- Clean affected area
- Apply 1 to 3 times daily
- May be covered with a sterile bandage
- If bandaged, let dry first

Other information

- Store at room temperature
- Avoid excessive heat

Inactive ingredients

- Water

DOSAGE AND ADMINISTRATION

ANTISEPTIC WIPE

- 2in x 2.4in / 5cm x 6cm